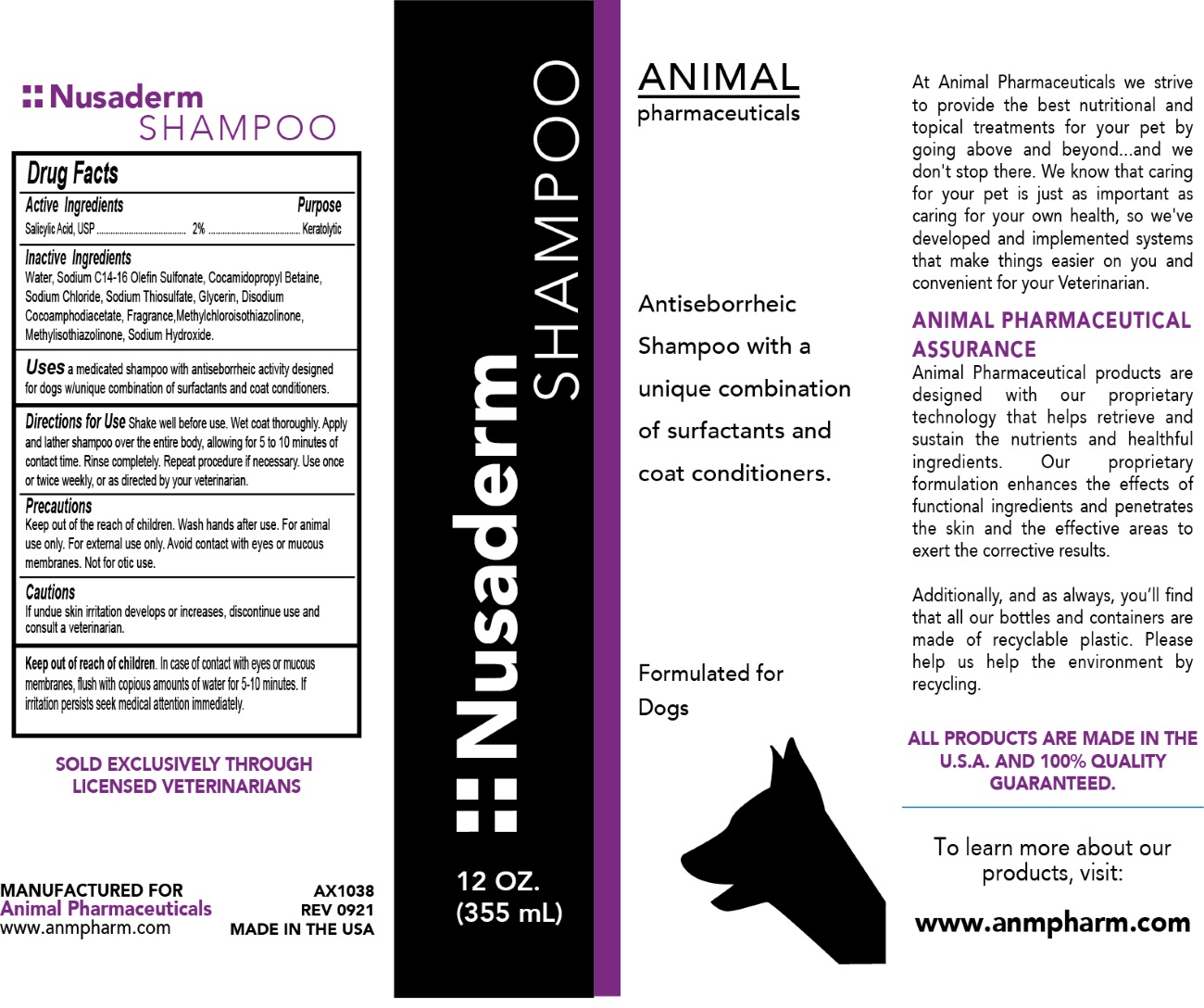 DRUG LABEL: Nusaderm
NDC: 68898-126 | Form: SHAMPOO
Manufacturer: Animal Pharmaceuticals
Category: animal | Type: OTC ANIMAL DRUG LABEL
Date: 20211020

ACTIVE INGREDIENTS: SALICYLIC ACID 2 g/100 mL
INACTIVE INGREDIENTS: WATER; SODIUM C14-16 OLEFIN SULFONATE; COCAMIDOPROPYL BETAINE; SODIUM CHLORIDE; SODIUM THIOSULFATE; GLYCERIN; DISODIUM COCOAMPHODIACETATE; METHYLCHLOROISOTHIAZOLINONE; METHYLISOTHIAZOLINONE; SODIUM HYDROXIDE

Nusaderm SHAMPOO

Active Ingredients

Salicylic Acid, USP 2%

Purpose

Keratolytic

Inactive Ingredients

Water, Sodium C14-16 Olefin Sulfonate, Cocamidopropyl Betaine, Sodium Chloride, Sodium Thiosulfate, Glycerin, Disodium Cocoamphodiacetate, Fragrance, Methylchloroisothiazolinone, Methylisothiazolinone, Sodium Hydroxide.

Uses

a medicated shampoo with antiseborrheic activity designed for dogs with unique combination of surfactants and coat conditioners.

Directions for Use

Shake well before use. Wet coat thoroughly. Apply and lather shampoo over the entire body, allowing for 5 to 10 minutes of contact time. Rinse completely. Repeat procedure if necessary. Use once or twice weekly, or as directed by your veterinarian.

Precautions

Keep out of the reach of children. Wash hands after use. For animal use only. For external use only. Avoid contact with eyes or mucous membranes. Not for otic use.

Cautions

If undue skin irritation develops or increases, discontinue use and consult a veterinarian.

Keep out of reach of children. In case of contact with eyes or mucous membranes, flush with copious amounts of water for 5-10 minutes. If irritation persists seek medical attention immediately.

Antiseborrheic Shampoo with a unique combination of surfactants and coat conditioners.

Formulated for Dogs

At Animal Pharmaceuticals we strive to provide the best nutritional and topical treatments for your pet by going above and beyond...and we don't stop there. We know that caring for your pet is just as important as caring for your own health, so we've developed and implemented systems that make things easier on you and convenient for your Veterinarian.

ANIMAL PHARMACEUTICAL ASSURANCE
Animal Pharmaceutical products are designed with our proprietary technology that helps retrieve and sustain the nutrients and healthful ingredients. Our proprietary formulation enhances the effects of functional ingredients and penetrates the skin and the effective areas to exert the corrective results.

Additionally, and as always, you'll find that all our bottles and containers are made of recyclable plastic. Please help us help the environment by recycling.

ALL PRODUCTS ARE MADE IN THE U.S.A. AND 100% QUALITY GUARANTEED.

To learn more about our products, visit:

www.anmpharm.com

SOLD EXCLUSIVELY THROUGH LICENSED VETERINARIANS

MANUFACTURED FOR
Animal Pharmaceuticals

MADE IN THE USA